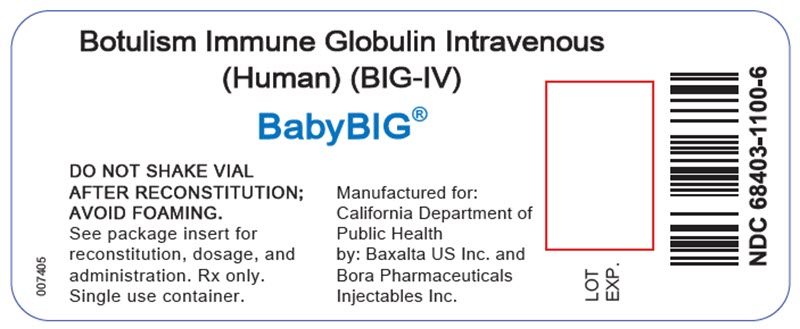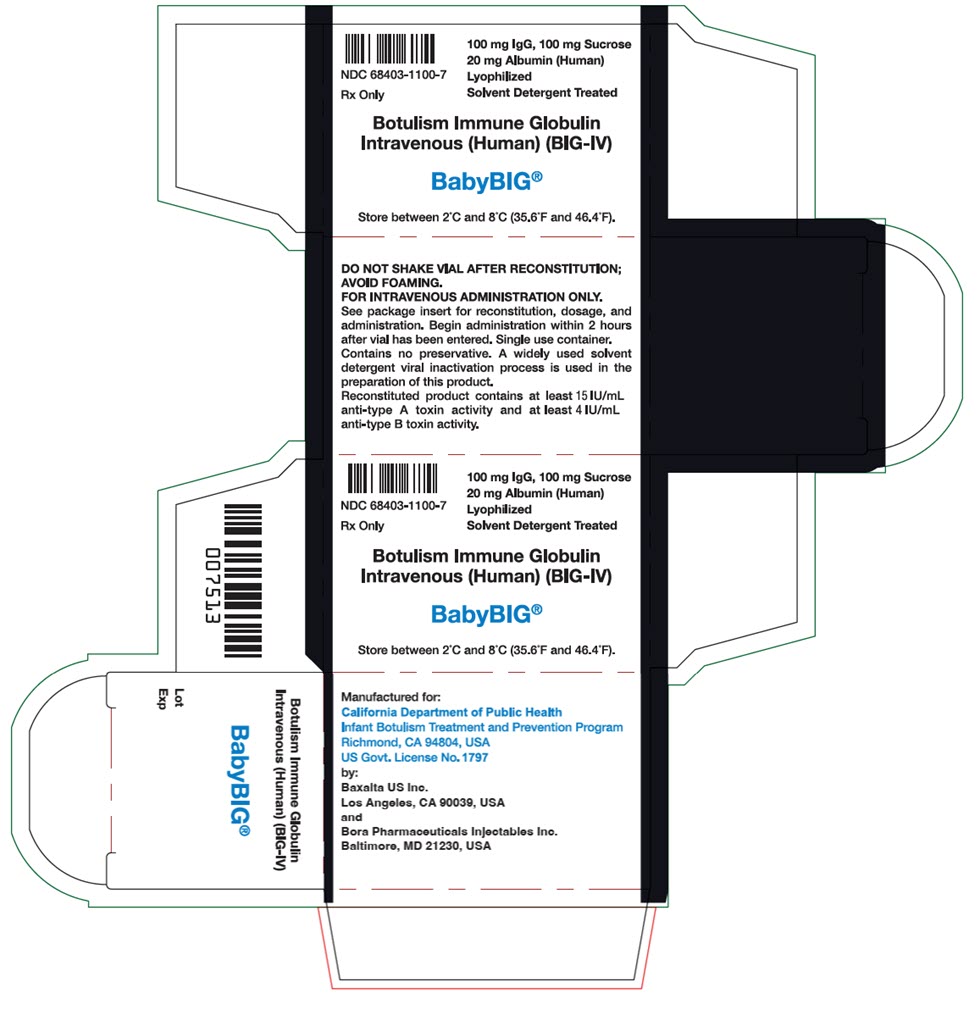 DRUG LABEL: BabyBIG
NDC: 68403-1100 | Form: INJECTION, POWDER, LYOPHILIZED, FOR SOLUTION
Manufacturer: CALIFORNIA DEPARTMENT OF PUBLIC HEALTH
Category: prescription | Type: HUMAN PRESCRIPTION DRUG LABEL
Date: 20251208

ACTIVE INGREDIENTS: human botulinum neurotoxin a/b immune globulin 50 mg/1 mL
INACTIVE INGREDIENTS: sucrose 50 mg/1 mL; albumin human 10 mg/1 mL; sodium phosphate, monobasic, anhydrous

HIGHLIGHTS OF PRESCRIBING INFORMATION

These highlights do not include all the information needed to use BabyBIG, [Botulism Immune Globulin Intravenous (Human)], safely and effectively. See full prescribing information for BabyBIG.
BabyBIG [Botulism Immune Globulin Intravenous (Human) (BIG-IV)]
Lyophilized Powder for Reconstitution and Injection
Initial U.S. Approval: 2003

RECENT MAJOR CHANGES

Drug Interactions (7) | 06/2021

1 INDICATIONS AND USAGE

BabyBIG is an immune globulin intravenous (human) indicated for:

- Treatment of infant botulism caused by toxin types A or B in patients below one year of age (1).

2 DOSAGE AND ADMINISTRATION

Intravenous use only (2)

- Recommended dose is 1.0 mL/kg (50 mg/kg) given as a single intravenous infusion (2).
- Reconstitute in 2 mL Sterile Water for Injection USP and initiate infusion within 2 hours of reconstitution (2.1).
- Administer BabyBIG through a separate intravenous line (2.3).
- Begin infusion slowly (0.5 mL/kg/h); if no untoward reaction in 15 minutes, increase rate to 1.0 mL/kg/h (2.2, 2.3).
- DO NOT EXCEED THE RECOMMENDED DOSE, CONCENTRATION, AND RATE OF INFUSION (2.3).

3 DOSAGE FORMS AND STRENGTHS

- Single-use vial of 100 mg ± 20 mg lyophilized immunoglobulin (3)
- Reconstitution as directed results in a BabyBIG solution concentration of 50 mg/mL (2.1)

4 CONTRAINDICATIONS

- Prior history of severe reaction to other human immunoglobulin preparations (4)
- Selective immunoglobulin A deficiency with anti-IgA antibodies (4)

5 WARNINGS AND PRECAUTIONS

- Assess renal function prior to and following administration (5.1, 5.2).
- Anaphylaxis and hypersensitivity reactions may occur (5.4). This risk should be considered when an IgA-deficient patient is to receive subsequent administration of blood products containing IgA after previous treatment with BabyBIG (4).
- Hyperproteinemia, increased serum viscosity and hyponatremia may occur in patients receiving immune globulin intravenous (human) (IGIV) therapy (5.6).
- Thrombotic events have occurred in patients receiving IGIV products. Monitor patients with known risk factors for thrombotic events; consider baseline assessment of blood viscosity for those at risk of hyperviscosity (5.7).
- Hemolytic anemia can develop subsequent to IGIV therapy due to enhanced RBC sequestration (5.8).
- IGIV recipients should be monitored for pulmonary adverse reactions, such as Transfusion-Related Acute Lung Injury (TRALI) (5.9).
- Aseptic meningitis syndrome (AMS) has been reported with other IGIV treatment, especially with high doses or rapid infusion (5.5).
- The product is made from human plasma and may contain infectious agents, e.g. viruses and, theoretically, the Creutzfeldt-Jakob disease agent (5.3).

6 ADVERSE REACTIONS

The most common adverse reaction occurring in at least 5% of the patients treated with BabyBIG in a controlled clinical study was mild and transient erythematous rash of the face or trunk (6.1).

To report SUSPECTED ADVERSE REACTIONS, contact the California Department of Public Health at 1-510-231-7600 and http://www.infantbotulism.org/ or FDA at 1-800-FDA-1088 or www.fda.gov/medwatch.

7 DRUG INTERACTIONS

- The passive transfer of antibodies may interfere with the response to live viral vaccines (7).

8 USE IN SPECIFIC POPULATIONS

- For use only in patients below one year of age (8.4)
- Renal impairment: Administer at minimum concentration and rate of infusion (2.3)

FULL PRESCRIBING INFORMATION

1 INDICATIONS AND USAGE

BabyBIG®, Botulism Immune Globulin Intravenous (Human), is indicated for the treatment of infant botulism caused by toxin type A or B in patients below one year of age.

2 DOSAGE AND ADMINISTRATION

For Intravenous Use Only

2.1 Preparation for Administration

- BabyBIG does not contain a preservative. After reconstitution of the lyophilized product, the vial should be entered only once for the purpose of administration, and the infusion should begin within 2 hours of reconstitution.
- Remove the tab portion of the vial cap and clean the rubber stopper with 70% alcohol or equivalent.
- Reconstitute the lyophilized powder with 2 mL of Sterile Water for Injection USP, to obtain a 50 mg/mL BabyBIG solution. A double-ended transfer needle or large syringe is suitable for adding the water for reconstitution. When using a double-ended transfer needle, insert one end first into the vial of water. The lyophilized powder is supplied in an evacuated vial; therefore, the water should transfer by suction (the jet of water should be aimed to the side of the vial). After the water is transferred into the evacuated vial, the residual vacuum should be released to hasten the dissolution.
- Rotate the container gently to wet all the powder. An approximately 30-minute interval should be allowed for dissolving the powder. DO NOT SHAKE THE VIAL, AS THIS WILL CAUSE FOAMING.
- Inspect BabyBIG visually for particulate matter and discoloration prior to administration. Infuse the solution only if it is colorless, free of particulate matter, and not turbid [see WARNINGS AND PRECAUTIONS (5)].
- To prevent the transmission of hepatitis viruses or other infectious agents from one person to another, use sterile disposable syringes and needles. Never reuse syringes and needles.

2.2 Treatment of Infant Botulism Caused by Toxin Type A or B

The recommended total dosage of BabyBIG is 1.0 mL/kg (50 mg/kg), given as a single intravenous infusion as soon as the clinical diagnosis of infant botulism is made. BabyBIG should be used with caution in patients with pre-existing renal insufficiency and in patients judged to be at increased risk of developing renal insufficiency (including, but not limited to, those with diabetes mellitus, volume depletion, paraproteinemia, sepsis, or who are receiving known nephrotoxic drugs) [see WARNINGS AND PRECAUTIONS (5.1)].

2.3 Administration

- Do not pre-dilute BabyBIG before infusion.
- Begin infusion within 2 hours after reconstitution is complete and conclude within 4 hours of reconstitution, unless infusion is temporarily interrupted for adverse reaction. Monitor vital signs continuously during infusion.
- Administer BabyBIG intravenously using low volume tubing and a constant infusion pump (i.e., an IVAC pump or equivalent) through a separate intravenous line. If a separate line is not possible, it may be "piggybacked" into a pre-existing line if that line contains either Sodium Chloride Injection USP, or one of the following dextrose solutions (with or without NaCl added): 2.5% dextrose in water, 5% dextrose in water, 10% dextrose in water, or 20% dextrose in water. If a pre-existing line must be used, do not dilute BabyBIG more than 1:2 with any of the above-named solutions. Admixtures of BabyBIG with any other solutions have not been evaluated. Use an in-line or syringe-tip sterile, disposable filter (18 μm) for the administration of BabyBIG.
- In the absence of prospective data allowing identification of the maximum safe dose, concentration, and rate of infusion in these patients, DO NOT EXCEED THE RECOMMENDED DOSE, CONCENTRATION, AND RATE OF INFUSION.
- Begin infusion slowly. Administer BabyBIG intravenously at 0.5 mL per kg body weight per hour (25 mg/kg/h). If no untoward reactions occur after 15 minutes, the rate may be increased to 1.0 mL/kg/h (50 mg/kg/h). DO NOT EXCEED THIS RATE OF ADMINISTRATION. Monitor the patient closely during and after each rate change [see WARNINGS AND PRECAUTIONS (5.1)]. At the recommended rates, infusion of the indicated dose should take 67.5 minutes total elapsed time.

Time (minutes) | Rate of 5% Solution | mg/kg/hr
0-15 | 0.5 mL/kg/h | 25
15 to end of infusion | 1.0 mL/kg/h | 50

- As adverse reactions experienced by patients treated with immune globulin intravenous (human) (IGIV) products have been related to the infusion rate, if the patient develops a minor side effect (i.e., flushing), slow the rate of infusion or temporarily interrupt the infusion. If anaphylaxis or a significant drop in blood pressure occurs, discontinue the infusion and administer epinephrine.

3 DOSAGE FORMS AND STRENGTHS

- 100 mg ± 20 mg lyophilized immunoglobulin per single-dose vial

4 CONTRAINDICATIONS

- As with other immunoglobulin preparations, BabyBIG should not be used in individuals with a prior history of severe reaction to other human immunoglobulin preparations.[1-4]
- Individuals with selective immunoglobulin A deficiency have the potential for developing antibodies to immunoglobulin A and could have anaphylactic reactions to the subsequent administration of blood products that contain immunoglobulin A.

5 WARNINGS AND PRECAUTIONS

Only administer BabyBIGas an intravenous infusion, since other routes of administration have not been evaluated. Do not use BabyBIG if the reconstituted solution is turbid [see DOSAGE AND ADMINISTRATION (2.1)].

5.1 Patient Monitoring for Administration

- Patients should be well hydrated prior to the initiation of the BabyBIG infusion.
- Assess renal function, including the measurement of blood urea nitrogen (BUN) or serum creatinine prior to the initial infusion of BabyBIG [see DOSAGE AND ADMINISTRATION (2)]. Periodic monitoring of renal function tests and urine output is particularly important in patients judged to have a potential risk for developing acute renal failure.[1-6] Increases in serum creatinine and BUN have been observed as soon as one to two days following treatment with other IGIV products.
- During administration, monitor the patient's vital signs continuously and observe the patient carefully for any associated symptoms.
- DO NOT EXCEED THE RECOMMENDED INFUSION RATE of 1 mL/kg/hour (50 mg/kg/h), and follow the infusion schedule closely [see DOSAGE AND ADMINISTRATION (2.3)]. If a patient develops an infusion reaction, slow the rate of infusion immediately or temporarily interrupt the infusion.

5.2 Renal Adverse Reactions

Other IGIV products have been reported to be associated with renal dysfunction, acute renal failure, osmotic nephrosis, and death.[5, 6] While these reports of renal dysfunction and acute renal failure have been associated with the use of many licensed IGIV products, those that contained sucrose as a stabilizer and were administered at daily doses of 400 mg/kg or greater have accounted for a disproportionate share of the total number.[5, 7] BabyBIG contains sucrose as a stabilizer. Patients predisposed to acute renal failure include those patients with any degree of pre-existing renal insufficiency, diabetes mellitus, volume depletion, sepsis, paraproteinemia, or who are receiving known nephrotoxic drugs. Especially in such patients, BabyBIG should be administered at the minimum concentration available and at the minimum rate of infusion practicable.[1-4]

5.3 Transmission of Blood-Borne Infectious Agents

BabyBIG is made from human plasma and, like other plasma products, carries the possibility for transmission of blood-borne viral agents and, theoretically, the Creutzfeldt-Jakob disease agent. The risk of transmission of recognized blood-borne viruses has been reduced by screening plasma donors for prior exposure to certain viruses, for the presence of certain viral infections, and by the viral inactivation and/or removal properties of the precipitation procedures used for the purification of BabyBIG [see DESCRIPTION (11)]. Despite these measures, some as yet unrecognized blood-borne infectious agents may not be inactivated by the manufacturing process; therefore, BabyBIG, like any other blood product, should be given only if a benefit is expected [see PATIENT COUNSELING INFORMATION (17)].

5.4 Anaphylaxis

- Severe reactions, such as angioedema and anaphylactic shock, although not observed during clinical trials with BabyBIG, are a possibility.[8, 9] Clinical anaphylaxis may occur even when the patient is not known to be sensitive to immune globulin products. A reaction may be related to the rate of infusion; therefore, carefully adhere to the infusion rates as outlined under "DOSAGE AND ADMINISTRATION (2.3)." If anaphylaxis or a drop in blood pressure occurs, discontinue the infusion and administer epinephrine.[1-4]
- Although acute systemic allergic reactions were not seen in clinical trials with BabyBIG, epinephrine should be available for treatment of acute allergic symptoms [see ADVERSE REACTIONS (6.1)]. If hypotension or anaphylaxis occurs, discontinue the administration of BabyBIG immediately and give supportive care as needed.

5.5 Aseptic Meningitis Syndrome

- An aseptic meningitis syndrome (AMS) has been reported to occur infrequently in association with IGIV administration.[10-13] The syndrome usually begins within several hours to two days following IGIV treatment. It is characterized by symptoms and signs that include the following: severe headache, nuchal rigidity, drowsiness, fever, photophobia, painful eye movements, and nausea and vomiting. Cerebrospinal fluid studies are frequently positive with pleocytosis up to several thousand cells per cubic millimeter, predominately from the granulocytic series, and with elevated protein levels up to several hundred mg/dL. Conduct a thorough neurological examination in patients exhibiting such symptoms and signs to rule out other causes of meningitis.[10-13] AMS may occur more frequently in association with high total doses (2 g/kg) of IGIV treatment. Discontinuation of IGIV treatment has resulted in remission of AMS within several days without sequelae.[1, 10-13] AMS was not observed in clinical trials of BabyBIG.

5.6 Hyperproteinemia, Hyponatremia, and Serum Viscosity

Hyperproteinemia, hyponatremia, and increased serum viscosity have been observed following administration of IGIV products. It is clinically critical to distinguish true hyponatremia from pseudohyponatremia caused by decreased calculated serum osmolality or elevated osmolar gap, because treatment aimed at decreasing serum free water in patients with pseudohyponatremia may lead to volume depletion, a further increase in serum viscosity and a higher risk of thromboembolic events. These adverse events have not been observed with BabyBIG.

5.7 Thrombotic Events

Thrombotic events may occur following IGIV treatment. Patients at risk may include those with a history of atherosclerosis, multiple cardiovascular risk factors, advanced age, impaired cardiac output, coagulation disorders, prolonged periods of immobilization, and/or known or suspected hyperviscosity. Consider baseline assessment of blood viscosity in patients at risk for hyperviscosity, including those with cryoglobulins, fasting chylomicronemia/markedly high triacylglycerols (triglycerides), or monoclonal gammopathies. For patients judged to be at risk of developing thrombotic events, administer BabyBIG at the minimum rate of infusion practicable.

5.8 Hemolytic Anemia

IGIV products may contain blood group antibodies, which can act as hemolysins and induce in vivo coating of red blood cells with immunoglobulin, causing a positive direct antiglobulin reaction and, rarely, hemolysis. Hemolytic anemia may develop subsequent to IGIV therapy due to enhanced red blood cell sequestration.

Monitor patients for clinical signs and symptoms of hemolysis. If these are present after BabyBIG infusion, perform appropriate confirmatory laboratory testing.

5.9 Transfusion-Related Acute Lung Injury (TRALI)

Non-cardiogenic pulmonary edema may occur in patients following IGIV treatment.[14] TRALI is characterized by severe respiratory distress, pulmonary edema, hypoxemia, normal left ventricular function, and fever. Symptoms typically occur within 1 to 6 hours following treatment [See PATIENT COUNSELING INFORMATION (17)].

Monitor patients for pulmonary adverse reactions. If TRALI is suspected, perform appropriate tests for the presence of anti-neutrophil antibodies in both the product and patient serum.

TRALI may be managed using oxygen therapy with adequate ventilatory support.

6 ADVERSE REACTIONS

- Serious adverse reactions were not observed in clinical trials using BabyBIG.
- The most common adverse reaction observed with BabyBIG treatment during clinical trials (>5%) was skin rash.
- Other reactions such as chills, muscle cramps, back pain, fever, nausea, vomiting, and wheezing were the most frequent adverse reactions observed during the clinical trials of similarly-prepared human IGIV products.[15] The incidence of these reactions was less than 5% of all infusions in BabyBIG clinical trials, and these reactions were most often related to infusion rates.[7]

6.1 Clinical Trials Experience

Because clinical trials are conducted under widely varying conditions, adverse reaction rates observed in the clinical trials of a drug cannot be directly compared to rates in the clinical trials of another drug and may not reflect the rates observed in clinical practice.

Two clinical studies of BabyBIG were performed: (1) an adequate and well-controlled study to evaluate safety and efficacy of BabyBIG, which used BabyBIG Lot 1, and (2) an open label study to collect additional safety data and confirm efficacy, which used BabyBIG Lot 2 [see CLINICAL STUDIES (14)].[16, 17] Different methodologies were used to collect adverse events in the controlled study and open label study. Minor clinical events that were not recorded as adverse events in the controlled study were recorded as adverse events in the open label study.

The only adverse event considered possibly related to BabyBIG administration was a mild, transient erythematous rash of the face or trunk. The following table summarizes the occurrence of rash by day of study relative to day of treatment for the randomized, controlled clinical trial (RCT) and for the open label study (OLS).

Day of Study Relative to Treatment |  | RCT |  | OLS
Day of Study Relative to Treatment |  | Placebo [Both Gammagard 5% and Gammagard S/D 5% were used as placebo in this study.] (N=64) | BabyBIG (N=65) | BabyBIG (N=293)
Day of Study Relative to Treatment |  | n (%)
Day -5 |  | 0 (0) | 1 (2) | 6 (2)
Day -4 |  | 2 (3) | 1 (2) | 5 (2)
Day -3 |  | 3 (5) | 4 (6) | 6 (2)
Day -2 |  | 5 (8) | 2 (3) | 22 (8)
Day -1 |  | 4 (6) | 11 (17) | 28 (10)
Day 0 [Day 0 is the day of treatment.] | Before [In reference to treatment.] | 5 (8) | 9 (14) | 32 (11)
Day 0 [Day 0 is the day of treatment.] | During & After | 2 (3) | 9 (14) | 39 (13)
Day +1 |  | 2 (3) | 1 (2) | 18 (6)
Day +2 |  | 1 (2) | 2 (3) | 13 (4)
Day +3 |  | 3 (5) | 0 (0) | 7 (2)
Day +4 |  | 1 (2) | 2 (3) | 11 (4)
Day +5 |  | 2 (3) | 0 (0) | 5 (2)

In the controlled study, when only treatment emergent events are considered, 14% of the BabyBIG-treated patients experienced erythematous rash during or after study infusion. Eight percent of placebo-treated patients also experienced erythematous rash in this study. A similar rash is known to occur both in infant botulism patients who have not received any IGIV products[18] and in patients treated with other IGIVs,[2, 3] making it difficult to ascertain the causality of the rash.

In the controlled study only, the following adverse events occurred in at least 5% of the patients receiving BabyBIG or placebo:

Adverse Event | BabyBIG N=65 | Placebo [Both Gammagard 5% and Gammagard S/D 5% were used as placebo in this study.] N=64
Adverse Event | n (%)
N (%) of Patients with any AE | 20 (31) | 29 (45)
Rash erythematous | 9 (14) | 5 (8)
Otitis media | 7 (11) | 5 (8)
Pneumonia | 7 (11) | 9 (14)
Anemia | 3 (5) | 9 (14)
Hyponatremia | 3 (5) | 9 (14)
Hypertension | 1 (2) | 3 (5)
Respiratory arrest | 1 (2) | 6 (9)
Urinary tract infection | 1 (2) | 8 (13)
Convulsions | 0 | 3 (5)

In the open label study only, the following adverse events occurred in at least 5% of the patients:

Adverse Event | BabyBIG N=293 N (%)
Patients with Any AE | 285 (97)
Blood pressure increased | 221 (75)
Dysphagia | 190 (65)
Irritability | 121 (41)
Atelectasis | 113 (39)
Rhonchi | 100 (34)
Pallor | 83 (28)
Loose stools | 73 (25)
Dermatitis contact | 70 (24)
Rash erythematous | 64 (22)
Vomiting | 58 (20)
Nasal congestion | 54 (18)
Edema | 54 (18)
Oxygen saturation decreased | 51 (17)
Pyrexia | 51 (17)
Body temperature decreased | 48 (16)
Blood pressure decreased | 47 (16)
Cardiac murmur | 45 (15)
Cough | 39 (13)
Rales | 37 (13)
Abdominal distension | 33 (11)
Breath sounds decreased | 30 (10)
Dehydration | 30 (10)
Agitation | 29 (10)
Hemoglobin decreased | 27 (9)
Stridor | 26 (9)
Lower respiratory tract infection | 23 (8)
Oral candidiasis | 23 (8)
Injection-site reaction | 21 (7)
Tachycardia NOS | 20 (7)
Peripheral coldness | 19 (7)
Dyspnea NOS | 16 (6)
Hyponatremia | 16 (6)
Injection-site erythema | 15 (5)
Intubation NOS | 15 (5)
Metabolic acidosis | 15 (5)
Neurogenic bladder | 15 (5)
Anemia | 14 (5)
Tachypnea | 14 (5)

Adverse event coding was used in the open label study to distinguish between minor clinical events that required no intervention and more significant events that required intervention. For example, "increased blood pressure" or "decreased blood pressure" was assigned when transient changes in blood pressure were observed, whereas "hypertension" or "hypotension" was assigned when more prolonged or significant changes were observed.

6.2 Postmarketing Experience

Because postmarketing reporting of adverse reactions is voluntary and from a population of uncertain size, it is not always possible to reliably estimate the frequency of these reactions or establish a causal relationship to product exposure.

Experience with BabyBIG. No adverse reactions have been identified or reported that are ascribed to the use of BabyBIGduring postapproval use. Retrospective publications have shown safety-related information consistent with the safety-related information in the approved product labeling, and no new safety-related information has been presented for BabyBIG.[19, 20]

Experience with Other IGIV Products. Some classes of adverse reactions that have not been reported in BabyBIG clinical studies or postmarketing experience have been observed with the overall post-approval use of other IGIV products, as shown in the following table.

Respiratory | Apnea, Acute Respiratory Distress Syndrome (ARDS), Transfusion Related Acute Lung Injury (TRALI), cyanosis, hypoxemia, pulmonary edema, dyspnea, bronchospasm
Cardiovascular | Cardiac arrest, thromboembolism, vascular collapse, hypotension
Neurological | Coma, loss of consciousness, seizures, tremor
Integumentary | Steven-Johnson syndrome, epidermolysis, erythema multiforme, bullous dermatitis
Hematologic | Pancytopenia, leukopenia, hemolysis, positive direct antiglobulin (Coombs') test
General /Body as a Whole | Pyrexia, rigors
Musculoskeletal | Back pain
Gastrointestinal | Hepatic dysfunction, abdominal pain

7 DRUG INTERACTIONS

- Admixtures of BabyBIG with other drugs have not been evaluated. It is recommended that BabyBIG be administered separately from other drugs or medications that the patient may be receiving [see DOSAGE AND ADMINISTRATION (2)].
- Antibodies present in immune globulin preparations may interfere with the immune response to live virus vaccines such as polio, measles, mumps, and rubella; therefore, vaccination with live virus vaccines such as MMR (measles, mumps, and rubella), MMRV (measles, mumps, rubella, and varicella), and monovalent varicella vaccines should be deferred until six months after administration of BabyBIG. This interval may be shortened if exposure to measles is likely. If such vaccinations were given shortly before or after BabyBIG administration, revaccination may be necessary.[21]

8 USE IN SPECIFIC POPULATIONS

8.4 Pediatric Use

BabyBIG has been studied for safety and efficacy only in patients below one year of age [see ADVERSE REACTIONS (6) and CLINICAL STUDIES (14)]. It has not been tested in other populations.

10 OVERDOSAGE

Although limited data are available, clinical experience with other immunoglobulin preparations suggests that the major manifestations would be those related to volume overload.[1]

11 DESCRIPTION

BabyBIG, Botulism Immune Globulin Intravenous (Human) (BIG-IV), is a solvent-detergent-treated, sterile, lyophilized powder of immunoglobulin G (IgG), stabilized with 5% sucrose and 1% albumin (human). It contains no preservative. The purified immunoglobulin is derived from pooled adult plasma from persons who were immunized with recombinant botulinum vaccine for serotypes A and B (rBV A/B) and selected for their high titers of neutralizing antibody against botulinum neurotoxins type A and B. All donors were tested and their sera found to be negative for antibodies against the human immunodeficiency virus and the hepatitis B and hepatitis C viruses.

The pooled plasma was fractionated by cold ethanol precipitation of the proteins according to the Cohn/Oncley method, modified to yield a product suitable for intravenous administration.[22, 23] Several steps in the manufacturing process have been validated for their ability to inactivate or remove viruses that may not have been detected in the Source Plasma.[1, 24-27] These include Cohn/Oncley fractionation (Fraction I through Supernatant III Filtrate); nanofiltration through one 75-nm and two 35-nm filters; and solvent/detergent viral inactivation. These viral reduction steps have been validated in a series of in vitro experiments for their capacity to inactivate and/or remove Human Immunodeficiency Virus type 1 (HIV-1) and the following model viruses: bovine viral diarrhea virus (BVDV) as a model for hepatitis C virus; mouse encephalomyelitis virus (MEMV) as a model for hepatitis A virus; and pseudorabies virus (PRV), feline calicivirus (FCV), and Sindbis virus to cover a wide range of physicochemical properties in the model viruses studied. Total mean log10 reductions range from 4.63 to greater than 16 log10 as shown in the following table.

Process Step | Mean Reduction Factor (log10)
Process Step | Enveloped Viruses (size in nm) |  |  |  | Non-Enveloped Viruses (size in nm)
Process Step | Sindbis (60-70) | HIV-1 (80-100) | PRV (120-200) | BVDV (40-60) | MEMV (22-30) | FCV (35-39)
Cohn/Oncley fractionation | 6.6 | > 9.44 | > 10.37 | 6.25 | 4.06 | Not done
Nanofiltration | ≥ 6.84 | Not done | Not done | ≥ 5.4 | Not done | ≥ 6.92
Solvent/detergent treatment | Not done | > 4.51 | > 5.53 | > 4.85 | 0.57 [Included hydrophobic chromatography after solvent/detergent treatment.] | Not done
Cumulative Reduction Factor (log10) | ≥ 13.44 | > 13.95 | > 15.9 | ≥ 16.5 | 4.63 | ≥ 6.92

Additional testing performed with bovine parvovirus (as a model for parvovirus B19) showed a mean cumulative reduction factor of greater than 7.34 log10 for Cohn/Oncley fractionation and solvent/detergent treatment followed by hydrophobic chromatography. A mean cumulative reduction factor of 2.55 log10 was observed for removal of porcine parvovirus by nanofiltration.

When reconstituted with Sterile Water for Injection USP, each cubic centimeter (milliliter) contains approximately 50 ± 10 mg immunoglobulin, primarily IgG, and trace amounts of IgA and IgM; 50 mg sucrose; 10 mg albumin (human); and approximately 20 × 10^-3 mEq sodium. The reconstituted solution should appear colorless and translucent [see DOSAGE AND ADMINISTRATION (2.1), WARNINGS AND PRECAUTIONS (5)].

12 CLINICAL PHARMACOLOGY

BabyBIG contains IgG antibodies from the immunized donors who contributed to the plasma pool from which the product was derived. The titer of antibodies in the reconstituted product against type A botulinum toxin is at least 15 IU/mL and against type B toxin is at least 4.0 IU/mL. For toxin types A and B, by definition, 1 IU of botulinum antitoxin neutralizes 10,000 intraperitoneal mouse LD50 of botulinum toxin. The titers of antibody against botulinum neurotoxins C, D, and E have not been determined. In the case of infants who may be exposed to botulinum neurotoxin type A or B, this product is expected to provide the relevant antibodies at levels sufficient to neutralize the expected levels of circulating neurotoxin.[16, 28]

12.1 Mechanism of Action

BabyBIG contains antibodies specific for botulinum neurotoxin types A and B that bind to and neutralize circulating toxin types A and B in the patient.

12.2 Pharmacodynamics

Formal studies on pharmacodynamics have not been conducted with BabyBIG.

12.3 Pharmacokinetics

Traditional pharmacokinetic studies of BabyBIG have not been performed. However, the following table summarizes the mean serum titer of the anti-A component of BabyBIG following administration.

Time | BabyBIG Lot 1 Anti-A Titer (mean ± S.D.) | BabyBIG Lot 2 Anti-A Titer (mean ± S.D.)
Time | mIU/mL
Day 1 | Not done | 537.1 ± 213.4
Week 2 | 106.7 ± 44.6 | 192.2 ± 71.2
Week 4 | 90.0 ± 39.2 | 155.5 ± 56.7
Week 8 | 54.9 ± 22.8 | 96.0 ± 33.2
Week 12 | 26.0 ± 20.5 | 61.4 ± 32.3
Week 16 | 15.6 ± 10.4 | 33.0 ± 22.3
Week 20 | 7.6 ± 6.6 | 19.3 ± 14.1
NOTE: 1 IU of anti-type A or anti-type B antibody neutralizes, by definition, 10^4 mouse LD50 of botulinum toxin.

The half-life of injected BabyBIG has been shown to be approximately 28 days in infants,[16] which is in agreement with existing data for other immunoglobulin preparations.[2, 16]

14 CLINICAL STUDIES

Two clinical studies in infant botulism were performed:[16] (1) an adequate and well-controlled study to evaluate the safety and efficacy of BabyBIG (N=129), and (2) an open label study to collect additional safety data and confirm efficacy (N=293). In the adequate and well-controlled clinical study, BabyBIG, given within the first 3 days of hospital admission to 59 patients with laboratory-confirmed infant botulism, has been shown to reduce the following:

 | Average Length in Weeks |  | p-value
 | Placebo [Both Gammagard 5% and Gammagard S/D 5% were used as placebo in this study.] N=63 | BabyBIG N=59 | p-value
Hospital stay | 5.7 | 2.6 | p<0.0001
Intensive Care Unit stay | 3.6 | 1.3 | p<0.01
Mechanical ventilation | 2.4 | 0.7 | p<0.05
Tube-feeding | 10.0 | 3.6 | p<0.01

Length of hospital stay was also analyzed by patient age in both the adequate and well-controlled study and in an open label study.

Age (days) | Mean Length of Hospital Stay in Weeks
Age (days) | Placebo [Both Gammagard 5% and Gammagard S/D 5% were used as placebo in this study.] N=63 | BabyBIG (RCT) N=59 | BabyBIG (OLS) N=206
0-60 | 3.8 (N=10) | 2.8 (N=10) | 2.0 (N=46)
61-120 | 5.6 (N=29) | 1.9 (N=17) | 2.0 (N=68)
>120 | 6.6 (N=24) | 3.0 (N=32) | 1.8 (N=92)
RCT = randomized clinical trial
OLS = open label study

The observed reduction in length of hospital stay was statistically significant (p<0.01) with the exception of the 0 to 60-day age stratum, where small patient numbers limited the statistical power.

Length of hospital stay was analyzed in the adequate and well-controlled study by race (white versus non-white):

Race | Mean Length of Hospital Stay in Weeks
Race | Placebo [Both Gammagard 5% and Gammagard S/D 5 % were used as placebo in this study.] | BabyBIG (RCT)
White | 6.3 (N=40) | 2.8 (N=35)
Non-white | 4.6 (N=23) | 2.4 (N=24)

Length of hospital stay was significantly reduced in both white and non-white patients (p=0.002).

BabyBIG has not been tested for safety and efficacy in adults.

15 REFERENCES

1. Cytogam®, cytomegalovirus immune globulin intravenous (human) (CMV-IGIV). 55th edition. Physician's Desk Reference. 2001, Montvale, New Jersey: Medical Economics Company, Inc. 1861-1863.
2. Immune globulin intravenous (human) Iveegam En IGIV. In: Physician Desk Reference. 55th Edition, Montvale, New Jersey. Medical Economics Company, Inc., 2001:816-820.
3. Immune globulin intravenous (human) (IGIV) Gammagard® S/D. 55th edition. Physician's Desk Reference. 2001, Montvale, New Jersey: Medical Economics Company, Inc. 812-815.
4. Immune globulin intravenous (human) Sandoglobulin® lyophilized preparation. In: Physician's Desk Reference. 55th Edition, Montvale, New Jersey. Medical Economics Company, Inc., 2001:2210-2213.
5. Perazella MA, Cayco AV. Acute renal failure and intravenous immune globulin: sucrose nephropathy in disguise? Am J Ther. 1998;5:399-403.
6. Cayco AV, Perazella MA, Hayslett JP. Renal insufficiency after intravenous immune globulin therapy: a report of two cases and an analysis of the literature. J Am Soc Nephrol. 1997;8:1788-1793.
7. Important Drug Warning ("Dear Doctor") letter. Center for Biologics Evaluation and Research, Food and Drug Administration; November 13 1998.
8. Denepoux S, Eibensteiner PB, Steinberger P, Vrtala S, Visco V, Weyer A, et al. Molecular characterization of human IgG monoclonal antibodies specific for major birch pollen allergen Bet v 1. Anti-allergen IgG can enhance the anaphylactic reaction. FEBS Lett. 2000;465:36-46.
9. Burks AW, Sampson HA, Buckley RH. Anaphylactic reactions after gamma globulin administration in patients with hypogammaglobulinemia. Detection of IgE antibodies to IgA. N Engl J Med. 1986;314:560-564.
10. Sekul EA, Cupler EJ, Dalakas MC. Aseptic meningitis associated with high-dose intravenous immunoglobulin therapy: frequency and risk factors. Ann Intern Med. 1994;121:259-262.
11. Kato E, Shindo S, Eto Y, Hashimoto N, Yamamoto M, Sakata Y, et al. Administration of immune globulin associated with aseptic meningitis. JAMA. 1988;259:3269-3270.
12. Casteels-Van Daele M, Wijndaele L, Hunninck K. Intravenous immunoglobulin and acute aseptic meningitis. N Engl J Med. 1990;323:614-615.
13. Scribner C, Kapit R, Philips E, Rickels N. Aseptic meningitis and intravenous immunoglobulin therapy. Ann Intern Med. 1994;121:305-306.
14. Rizk A, Gorson KC, Kenney L, Weinstein R. Transfusion-related acute lung injury after the infusion of IVIG. Transfusion. 2001;41(2):264-268.
15. Snydman DR, Werner BG, Tilney NL, Kirkman RL, Milford EL, Cho SI, et al. Final analysis of primary cytomegalovirus disease prevention in renal transplant recipients with cytomegalovirus immune globulin: comparison of the randomized and open-label trials. Transplant Proc. 1991;23:1357-1360.
16. Arnon SS, Schechter R, Maslanka SE, Jewell NP, Hatheway CL. Human botulism immune globulin for the treatment of infant botulism. N Engl J Med. 2006;354(5):462-471.
17. Arnon SS. Creation and development of the public service orphan drug Human Botulism Immune Globulin. Pediatrics. 2007;119(4):785-789.
18. Long SS, Gajewski JL, Brown LW, Gilligan PH. Clinical, laboratory, and environmental features of infant botulism in southeastern Pennsylvania. Pediatrics. 1985;75:935-941.
19. Tseng-Ong L, Mitchell WG. Infant botulism: 20 years' experience at a single institution. J Child Neurol. 2007;22(12):1333-1337.
20. Underwood K, Rubin S, Deakers T, Newth C. Infant botulism: a 30-year experience spanning the introduction of botulism immune globulin intravenous in the intensive care unit at Childrens Hospital Los Angeles. Pediatrics. 2007;120(6):e1380-e1385.
21. AAP Committee on Infectious Diseases. Report of the Committee on Infectious Diseases. 31st edition; ed. D.W. Kimberlin, M.T. Brady, and M.A. Jackson. 2018.
22. Siber GR, Syndman DR. Use of immune globulins in the prevention and treatment of infections. Curr Clin Top Infect Dis. 1992;12:208-256.
23. Berkman SA, Lee ML, Gale RP. Clinical uses of intravenous immunoglobins. Ann Intern Med. 1990;112:278-292.
24. Safety of therapeutic immune globulin preparations with respect to transmission of human T-lymphotropic virus type III/lymphadenopathy-associated virus infection. Morb Mortal Wkly Rep. 1986;35(14):231-233.
25. Wells MA, Wittek AE, Epstein JS, Marcus-Sekura C, Daniel S, Tankersley DL, et al. Inactivation and partition of human T-cell lymphotrophic virus, type III, during ethanol fractionation of plasma. Trans. 1986;26:210-213.
26. Horowitz B, Wiebe ME, Lippin A, Stryker MH. Inactivation of viruses in labile blood derivatives. I. Disruption of lipid-enveloped viruses by tri(n-butyl)phosphate detergent combinations. Transfusion. 1985;25:516-522.
27. Edwards CA, Piet MPJ, Chin S, Horowitz B. Tri(n-butyl) phosphate/detergent treatment of licensed therapeutic and experimental blood derivatives. Vox Sang. 1987;52:53-59.
28. Paton JC, Lawrence AL, Steven IM. Quantitation of Clostridium botulinum organisms and toxin in feces and presence of Clostridium botulinum toxin in the serum of an infant with botulism. J Clin Microbiol. 1983;17:13-15.

16 HOW SUPPLIED/STORAGE AND HANDLING

STORAGE AND HANDLING

- NDC 68403-1100-6, 100 mg ± 20 mg lyophilized immunoglobulin single-dose vial individually packaged in a carton.
- Store the vial containing the lyophilized product between 2° and 8°C (35.6° to 46.4°F). Do not store BabyBIG in the reconstituted state.
- Use reconstituted BabyBIG within 2 hours.
- Do not use beyond expiration date, and dispose unused product in accordance with local requirements.

17 PATIENT COUNSELING INFORMATION

- Discuss the risks and benefits of BabyBIG use with the patient's legal guardians, including the possibility of adverse reactions, e.g., hypersensitivity reactions such as anaphylaxis, as well as aseptic meningitis, TRALI, hemolysis, renal failure, and thrombosis [see WARNINGS AND PRECAUTIONS (5)].
- Inform patient's legal guardians that BabyBIG is made from human plasma and may contain infectious agents that can cause disease. While the risk of transmitting an infection has been reduced by screening plasma donors for prior exposure, testing donated plasma, and inactivating or removing certain viruses during manufacturing, the patient's guardian should report any symptoms that concern them [see WARNINGS AND PRECAUTIONS (5.3)].
- Inform patient's legal guardians that BabyBIG may interfere with immune response to live viral vaccines (e.g., MMR) and instruct them to notify the healthcare provider of this potential interaction when the patient is to receive vaccinations [see DRUG INTERACTIONS (7)].

For additional information concerning BabyBIG, contact:

Infant Botulism Treatment and Prevention Program
California Department of Public Health
850 Marina Bay Parkway, Room E-361
Richmond, California 94804
Telephone: 510-231-7600
US Govt. License No. 1797

Manufactured by:
Baxalta US Inc.
Los Angeles, CA 90039, USA; and
Bora Pharmaceuticals Injectables Inc.
Baltimore, MD 21230, USA

Distributed by:
FFF Enterprises
Temecula, CA 92590, USA

FFF Enterprises
Kernersville, NC 27284, USA

Distributed for:
Infant Botulism Treatment and Prevention Program
California Department of Public Health
850 Marina Bay Parkway, Room E-361
Richmond, CA 94804

Revised September 2025

007612

PRINCIPAL DISPLAY PANEL - 2 mL Vial Label

Botulism Immune Globulin Intravenous
(Human) (BIG-IV)

BabyBIG®

DO NOT SHAKE VIAL
AFTER RECONSTITUTION;
AVOID FOAMING.
See package insert for
reconstitution, dosage, and
administration. Rx only.
Single use container.

007405

Manufactured for:
California Department of
Public Health
by: Baxalta US Inc. and
Bora Pharmaceuticals
Injectables Inc.

LOT
EXP.

PRINCIPAL DISPLAY PANEL - 1 Single Use Vial Carton

NDC 68403-1100-7

Rx Only

100 mg IgG, 100 mg Sucrose
20 mg Albumin (Human)
Lyophilized
Solvent Detergent Treated

Botulism Immune Globulin
Intravenous (Human) (BIG-IV)

BabyBIG®

Store between 2°C and 8°C (35.6°F and 46.4°F).